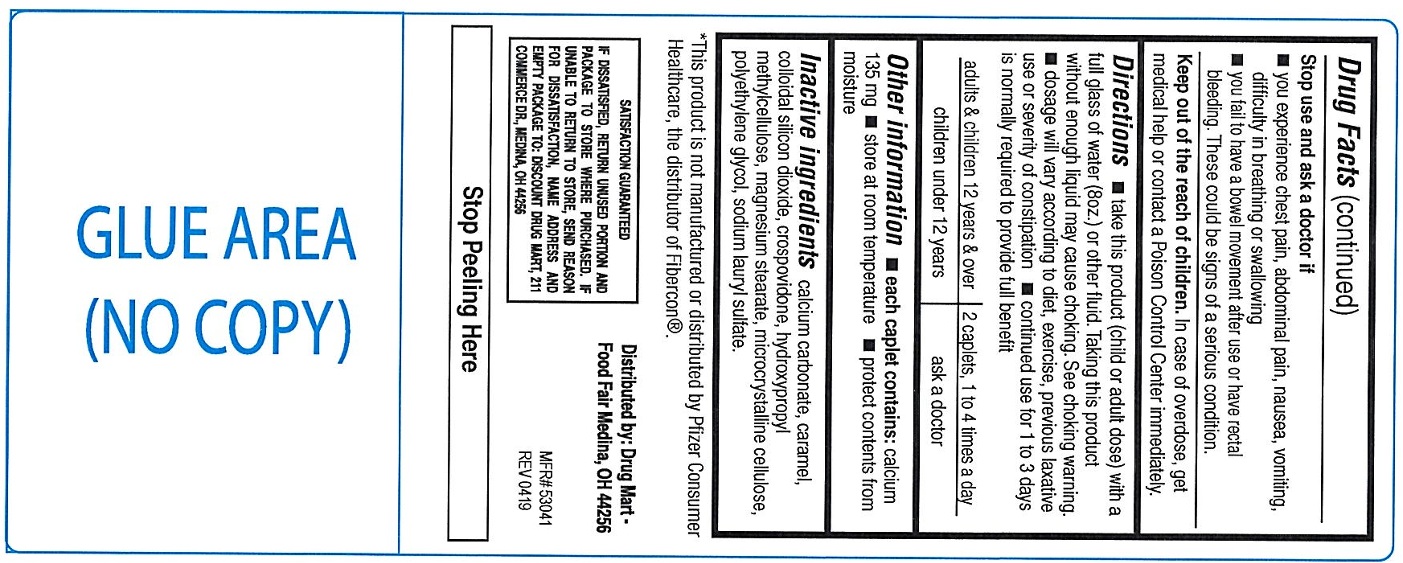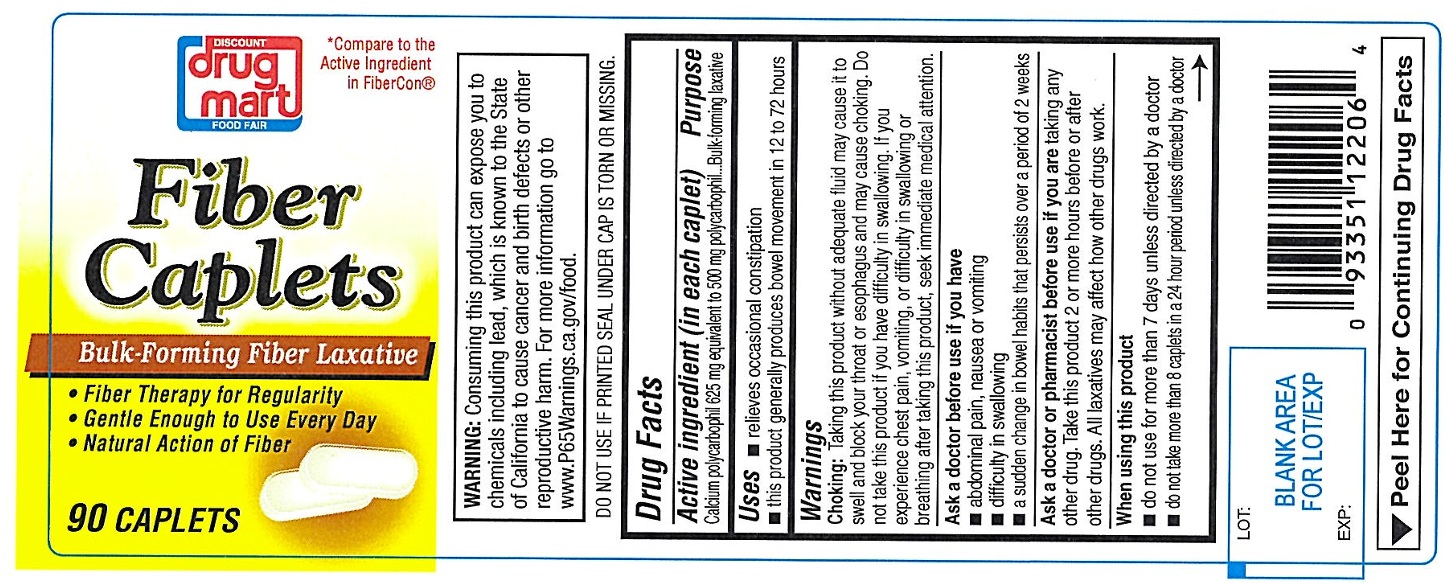 DRUG LABEL: Fiber laxative
NDC: 53943-147 | Form: TABLET
Manufacturer: Discount Drug Mart, Inc
Category: otc | Type: Human OTC Drug Label
Date: 20250227

ACTIVE INGREDIENTS: CALCIUM POLYCARBOPHIL 625 mg/1 1
INACTIVE INGREDIENTS: CALCIUM CARBONATE; CARAMEL; SILICON DIOXIDE; CROSPOVIDONE; HYPROMELLOSE, UNSPECIFIED; MAGNESIUM STEARATE; MICROCRYSTALLINE CELLULOSE; POLYETHYLENE GLYCOL, UNSPECIFIED; SODIUM LAURYL SULFATE

Bulk Forming Fiber Laxative

ACTIVE INGREDIENT (in each caplet)

Calcium polycarbophil 625 mg equivalent to 500 mg polycarbophil

PURPOSE

Bulk-forming laxative

USE(S)

- relieves occasional constipation
- this product generally produces bowel movement in 12 to 72 hours

WARNINGS

Choking: Taking this product without adequate fluid may cause it to swell and block your throat or esophagus and may cause choking. Do not take this product if you have difficulty in swallowing. If you experience chest pain, vomiting or difficulty in swallowing or breathing after taking this product, seek immediate medical attention.

ASK A DOCTOR BEFORE USE IF YOU HAVE

- abdominal pain, nausea or vomiting
- difficulty in swallowing
- a sudden change in bowel habits that persists over a period of 2 weeks

ASK A DOCTOR OR PHARMACIST BEFORE USE IF YOU ARE

taking any other drug. Take this product 2 or more hours before or after other drugs. All laxatives may affect how other drugs work.

WHEN USING THIS PRODUCT

- do not use for more than 7 days unless directed by a doctor
- do not take more than 8 caplets in a 24 hour period unless directed by a doctor

STOP USE AND ASK DOCTOR IF

- you experience chest pain, abdominal pain, nausea, vomiting, difficulty in breathing or swallowing
- you fail to have a bowel movement after use or have rectal bleeding. These could be signs of a serious condition.

KEEP OUT OF REACH OF CHILDREN.

In case of over dose, get medical help or contact a Poison Control Center immediately.

DIRECTIONS

- take this product (child or adult dose) with a full glass or water (8oz.) or other fluid. Taking this product without enough liquid may cause chocking. See choking warning.
- dosage will vary according to diet, exercise, previous laxative use or severity of constipation
- continued use for 1 to 3 days is normally required to provide full benefit

adults and children 12 years and over | 2 caplets, 1 to 4 times a day
children under 12 years | ask a doctor

OTHER INFORMATION

- each caplet contains: calcium 135 mg
- do not use if printed seal under cap is torn or missing
- store at room temperature
- protect contents from moisture

INACTIVE INGREDIENTS

calcium carbonate, caramel, colloidal silicon dioxide, crospovidone, hydroxypropyl methylcellulose, magnesium stearate, microcrystalline cellulose, polyethylene glycol, sodium lauryl sulfate.

PRINCIPAL DISPLAY PANEL

*Compare to the Active Ingredient in FiberCon®

DISCOUNT drug mart

FOOD FAIR

Fiber Caplets

Bulk - Forming Fiber Laxative

- Fiber Therapy for Regularity
- Gentle Enough to Use Every Day
- Natural Action of Fiber

90 Caplets